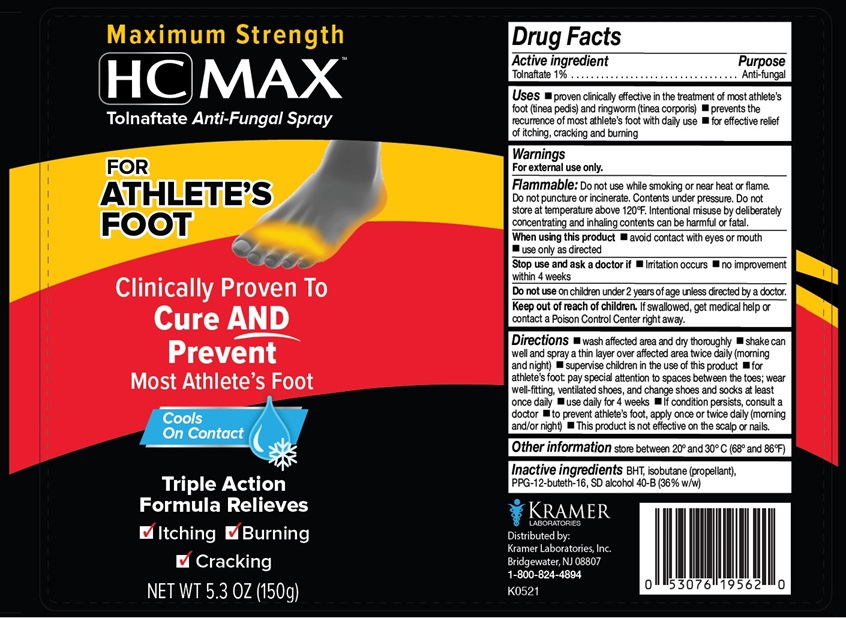 DRUG LABEL: HC Max Anti-Fungal
NDC: 55505-195 | Form: AEROSOL, SPRAY
Manufacturer: Kramer Laboratories
Category: otc | Type: HUMAN OTC DRUG LABEL
Date: 20251219

ACTIVE INGREDIENTS: Tolnaftate 1.5 g/150 g
INACTIVE INGREDIENTS: Butylated Hydroxytoluene; Isobutane; Ppg-12-Buteth-16; Alcohol

Drug Facts

ACTIVE INGREDIENT

Active ingredient | Purpose
Tolnaftate 1% | Anti-fungal

INDICATIONS AND USAGE

Uses ■ proven clinically effective in the treatment of most athlete’s foot (tinea pedis) and ringworm (tinea corporis) ■ prevents the recurrence of most athlete's foot with daily use ■ for effective relief of itching, cracking and burning

Warnings

For external use only.

WARNINGS

Flammable: Do not use while smoking or near heat or flame. Do not puncture or incinerate. Contents under pressure. Do not store at temperature above 120°F. Intentional misuse by deliberately concentrating and inhaling contents can be harmful or fatal.

When using this product ■ avoid contact with eyes or mouth ■ use only as directed

Stop use and ask a doctor if ■ Irritation occurs ■ no improvement within 4 weeks

Do not use on children under 2 years of age unless directed by a doctor.

Keep out of reach of children. If swallowed, get medical help or contact a Poison Control Center right away.

DOSAGE AND ADMINISTRATION

Directions ■ wash affected area and dry thoroughly ■ shake can well and spray a thin layer over affected area twice daily (morning and night) ■ supervise children in the use of this product ■ for athlete's foot: pay special attention to spaces between the toes; wear well-fitting, ventilated shoes, and change shoes and socks at least once daily ■ use daily for 4 weeks ■ if condition persists, consult a doctor ■ to prevent athlete's foot, apply once or twice daily (morning and/or night) ■ This product is not effective on the scalp or nails.

Other information store between 20º and 30º C (68º-86ºF)

INACTIVE INGREDIENT

Inactive ingredients BHT, isobutane (propellant), PPG-12-buteth-16, SD alcohol 40-B (36% w/w)

PRINCIPAL DISPLAY PANEL

Maximum Strength
HC MAX™
Tolnaftate Anti-Fungal Spray
FOR
ATHLETE'S
FOOT
Clinically Proven To
Cure AND
Prevent
Most Athlete's Foot
Cools
On Contact
Triple Action
Formula Relieves
✓ Itching
✓ Burning
✓ Cracking
NET WT 5.3 OZ (150 g)
KRAMER
LABORATORIES
Distributed by:
Kramer Laboratories, Inc.
Bridgewater, NJ 08807
1-800-824-4894
K0521